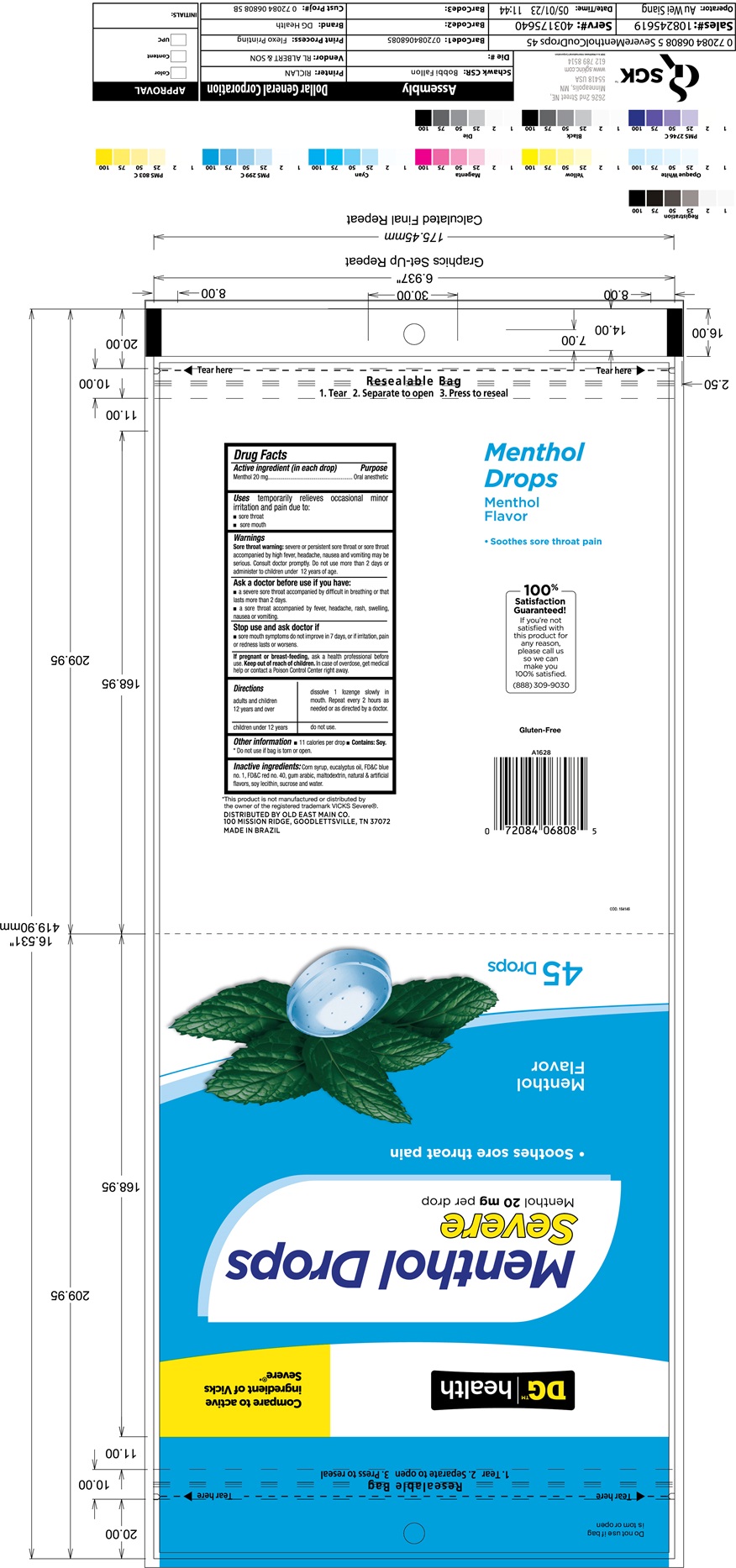 DRUG LABEL: Menthol Drops Dollar General Severe 45ct
NDC: 75712-040 | Form: LOZENGE
Manufacturer: Dollar General Corporation
Category: otc | Type: HUMAN OTC DRUG LABEL
Date: 20251024

ACTIVE INGREDIENTS: LEVOMENTHOL 20 mg/1 1
INACTIVE INGREDIENTS: SUCROSE; CORN SYRUP; EUCALYPTOL; FD&C BLUE NO. 1; FD&C RED NO. 40; ACACIA; MALTODEXTRIN; LECITHIN, SOYBEAN

Active ingredient

Menthol 20 mg

Purpose

Oral anesthetic

Uses

Temporarily relieves occasional minor irritation and pain due to: sore throat; sore mouth

Warnings

Sore throat warning: ore throat warning: severe or persistent sore throat or sore throat accompanied by high fever, headache, nausea and vomiting may be serious. Consult doctor promptly. Do not use more than 2 days or administer to children under 12 years of age.

Ask a doctor before use if you have:

- a severe sore throat accompanied by difficult in breathing or that lasts more than 2 days
- a sore accompanied by fever, headache, rash, swelling, nausea or vomiting

Stop use and ask a doctor if

- sore mouth symptoms do not improve in 7 days, or if irritation, pain or redness lasts or worsens

If pregnant or breast-feeding
ask a health professional before use.

Keep out of reach of children.

In case of overdose, get medical gelp or contact a Poison Control Center right away

Directions

adults and children 12 years and over | dissolve 1 lozenge slowly in mouth. Repeat every 2 hours as needed or as directed by a doctor.
children under 12 years | do not use

Other information

- 11 calories per drop
- do not use if bags is torn or open
- Contains: Soy

Inactive ingredients

Corn Syrup; eucalytus oil; FD&C blue no. 1; FD&C red no. 40; Gum Arabic; Maltodextrin; natural flavor; soy lecithin; sucrose and water